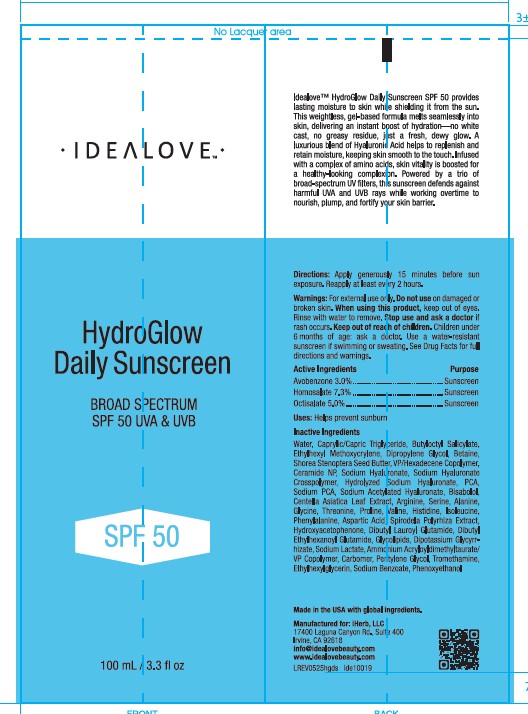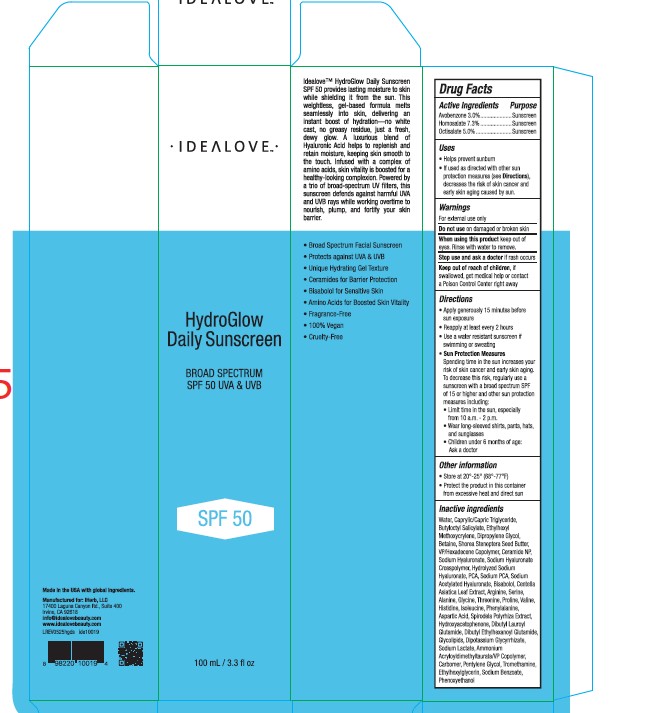 DRUG LABEL: IDEALOVE HYDROGLOW DAILY SUNSCREEN SPF 50
NDC: 68577-233 | Form: CREAM
Manufacturer: COSMAX USA, CORP
Category: otc | Type: HUMAN OTC DRUG LABEL
Date: 20251231

ACTIVE INGREDIENTS: OCTISALATE 5 mg/100 mL; HOMOSALATE 7.3 mg/100 mL; AVOBENZONE 3 mg/100 mL
INACTIVE INGREDIENTS: ARGININE; VP/HEXADECENE COPOLYMER; CARBOMER; PSEUDOMONAS GLUCOSE FERMENTATION RHAMNOLIPIDS; HYDROXYACETOPHENONE; ALANINE; TROMETHAMINE; DIPOTASSIUM GLYCYRRHIZATE; DIPROPYLENE GLYCOL; SPIRODELA POLYRHIZA; ETHYLHEXYLGLYCERIN; PCA; WATER; BUTYLOCTYL SALICYLATE; PENTYLENE GLYCOL; VALINE; ETHYLHEXYL METHOXYCRYLENE; SHOREA STENOPTERA SEED BUTTER; PHENOXYETHANOL; DIBUTYL LAUROYL GLUTAMIDE; SODIUM LACTATE; AMMONIUM ACRYLOYLDIMETHYLTAURATE/VP COPOLYMER; ASPARTIC ACID; DIBUTYL ETHYLHEXANOYL GLUTAMIDE; SERINE; HISTIDINE; PHENYLALANINE; BETAINE; THREONINE; PROLINE; CENTELLA ASIATICA LEAF; SODIUM HYALURONATE; GLYCINE; CAPRYLIC/CAPRIC TRIGLYCERIDE; SODIUM PCA; SODIUM ACETYLATED HYALURONATE; CERAMIDE NP; SODIUM BENZOATE; BISABOLOL; ISOLEUCINE

IDEALOVE HYDROGLOW DAILY SUNSCREEN SPF 50

Active Ingredients

Avobenzone 3.0%

Homosalate 7.3%

Octisalate 5.0%

Purpose

Sunscreen

USES

• Helps prevent sunburn • If used as directed with other sun, protection measures (see Directions), decreases the risk of skin cancer and early skin aging caused by sun.

Warnings

For external use only

Do not use on damaged or broken skin

When using this product keep out of eyes. Rinse with water to remove.

Stop use and ask a doctor if rash occurs.

Keep out of reach of children, if swallowed, get medical help or contact a Poison Control Center right away

DIRECTIONS

• Apply generously 15 minutes before sun exposure

• Reapply at least every 2 hours

• Use a water resistant sunscreen if swimming or sweating

• Sun Protection Measures

Spending time in the sun increases your risk of skin cancer and early skin aging.

To decrease this risk, regularly use a sunscreen with a broad spectrum SPF of 15 or higher and other sun protection measures including:

• Limit time in the sun, especially from 10 a.m. - 2 p.m.

• Wear long-sleeved shirts, pants, hats, and sunglasses

• Children under 6 months of age: Ask a doctor.

OTHER INFORMATION

• Store at 20°-25° (68°-77°F)

• Protect the product in this container from excessive heat and direct sun

Inactive ingredients

Water, Caprylic/Capric Triglyceride, Butyloctyl Salicylate, Ethylhexyl Methoxycrylene, Dipropylene Glycol, Betaine, Shorea Stenoptera Seed Butter, VP/Hexadecene Copolymer, Ceramide NP, Sodium Hyaluronate, Sodium Hyaluronate Crosspolymer, Hydrolyzed Sodium Hyaluronate, PCA, Sodium PCA, Sodium Acetylated Hyaluronate, Bisabolol, Centella Asiatica Leaf Extract, Arginine, Serine, Alanine, Glycine, Threonine, Proline, Valine, Histidine, Isoleucine, Phenylalanine, Aspartic Acid, Spirodela Polyrhiza Extract, Hydroxyacetophenone, Dibutyl Lauroyl Glutamide, Dibutyl Ethylhexanoyl Glutamide, Glycolipids, Dipotassium Glycyrrhizate, Sodium Lactate, Ammonium Acryloyldimethyltaurate/VP Copolymer, Carbomer, Pentylene Glycol, Tromethamine, Ethylhexylglycerin, Sodium Benzoate, Phenoxyethanol.

PACKAGE LABEL

Idealove - HydroGlow Daily Sunscreen SPF 50 BROAD SPECTRUM SPF 50 UVA & UVB - 100 mL / 3.3 fl oz